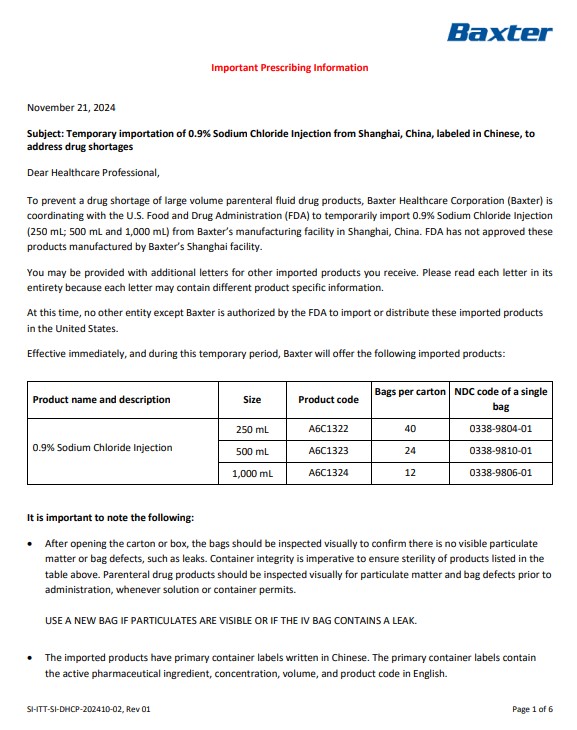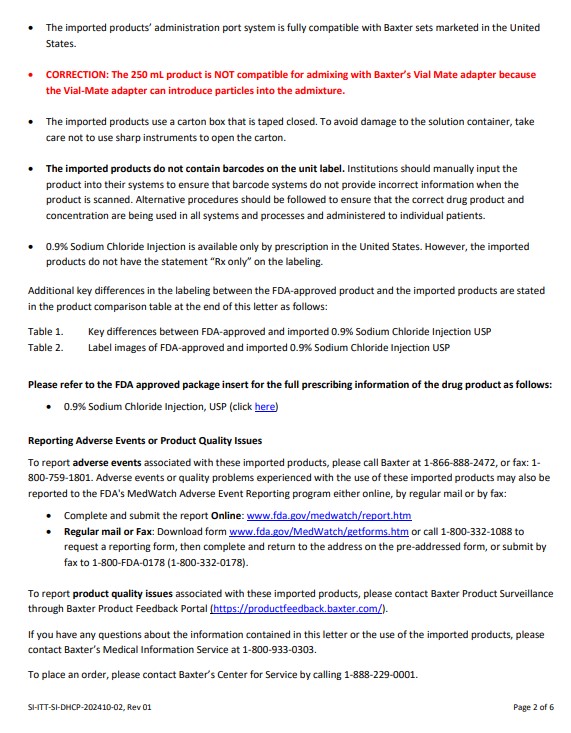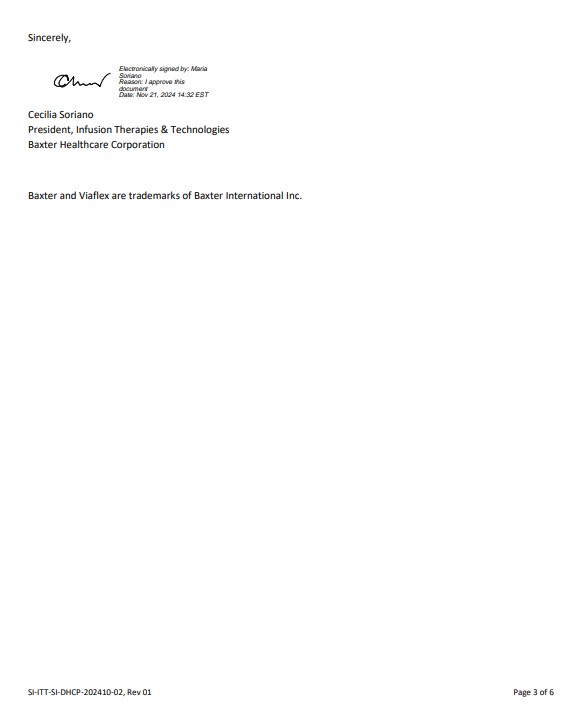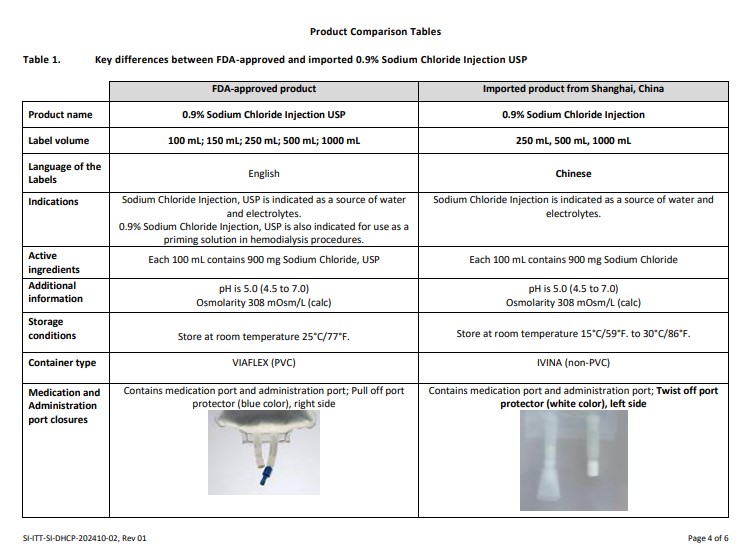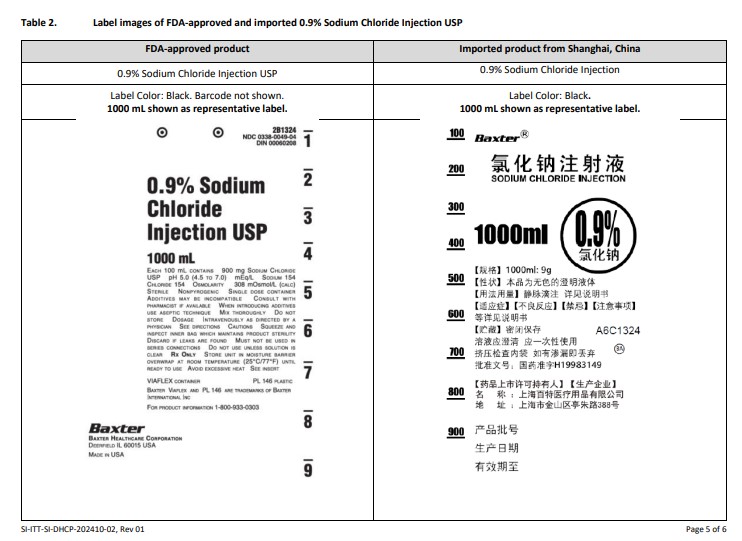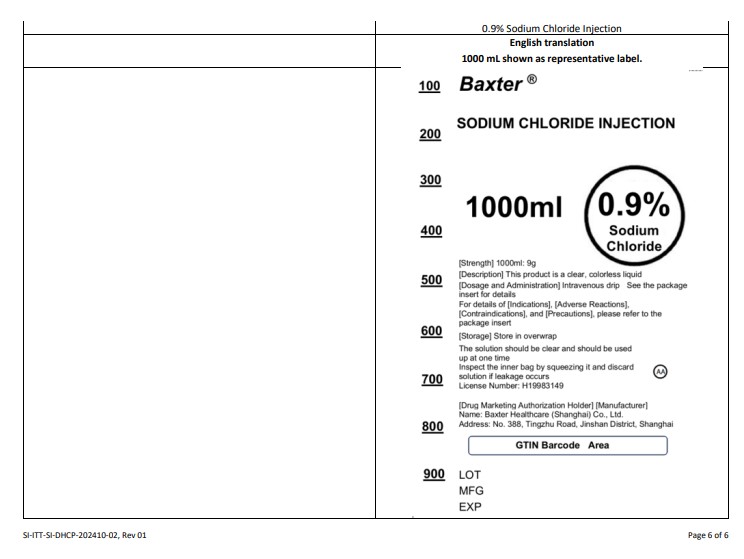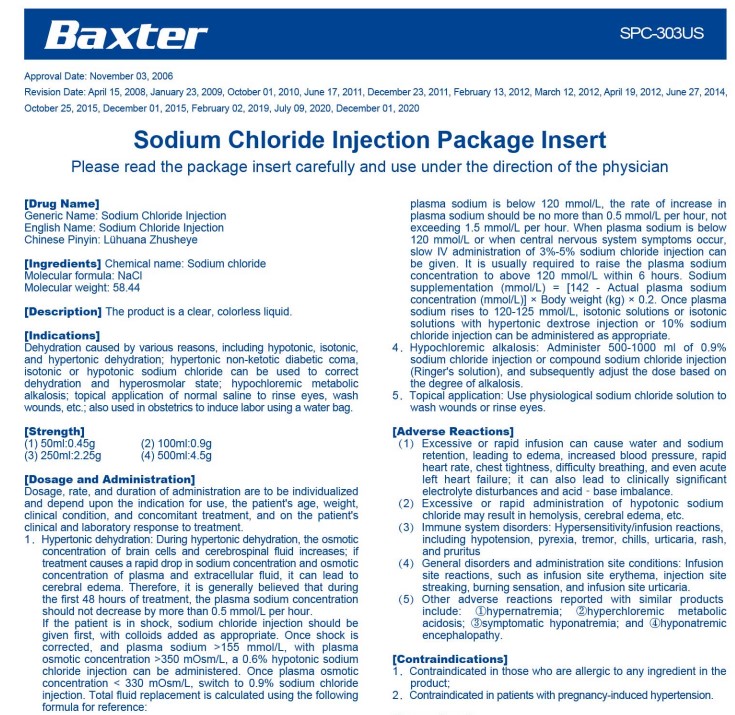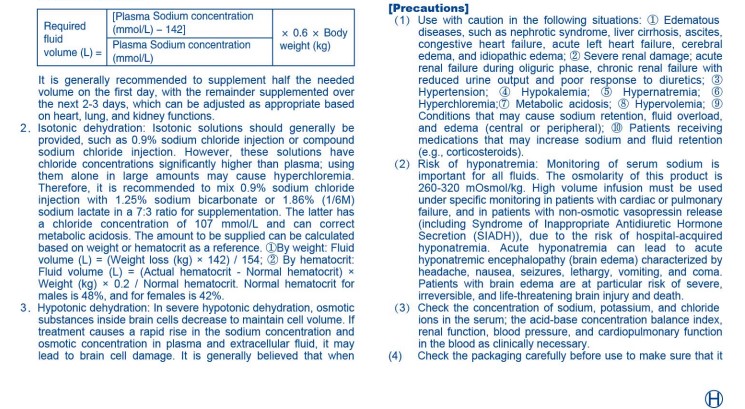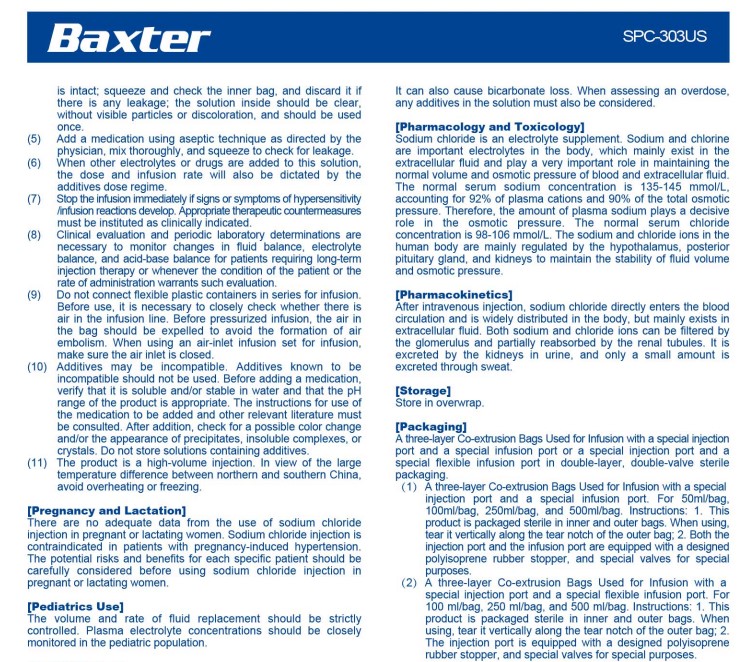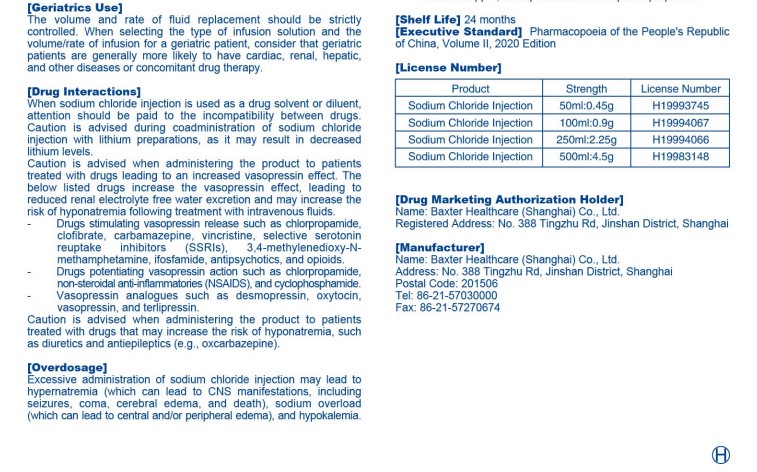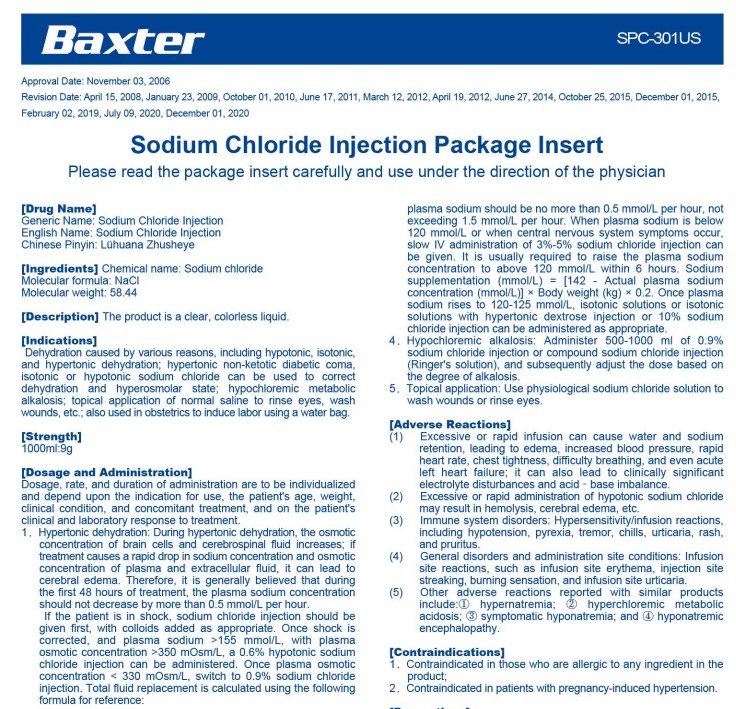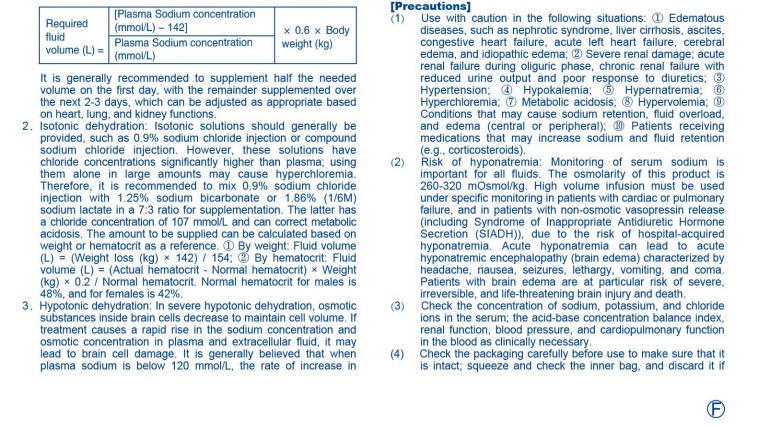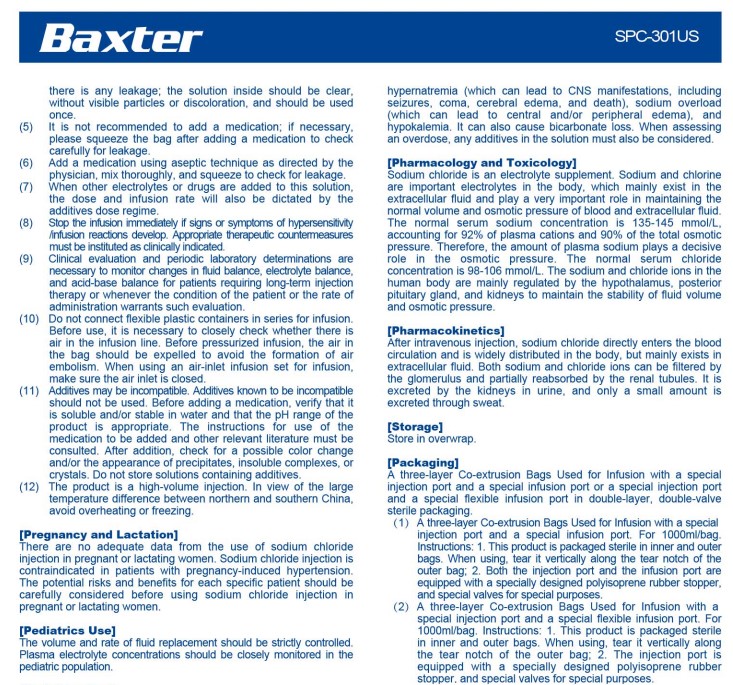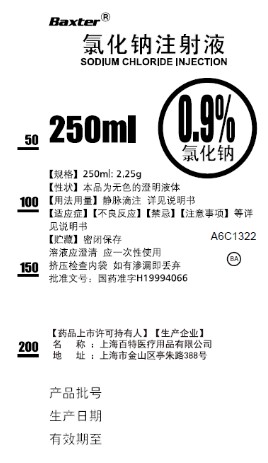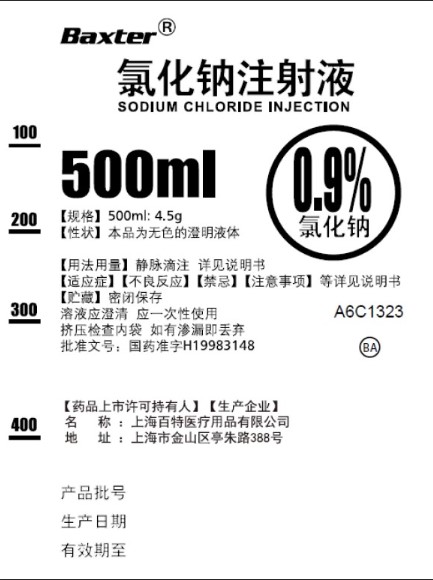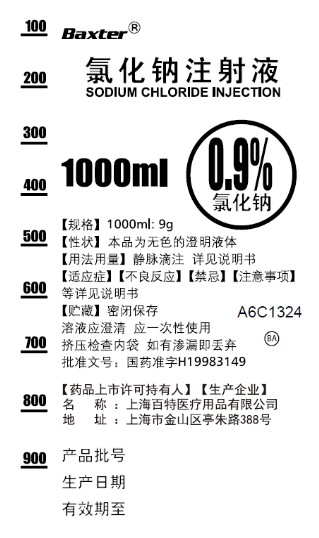 DRUG LABEL: Sodium Chloride
NDC: 0338-9804 | Form: INJECTION, SOLUTION
Manufacturer: Baxter Healthcare Corporation
Category: prescription | Type: HUMAN PRESCRIPTION DRUG LABEL
Date: 20241121

ACTIVE INGREDIENTS: SODIUM CHLORIDE 9 g/1000 mL
INACTIVE INGREDIENTS: WATER

0.9% Sodium Chloride Injection

HEALTH CARE PROFESSIONAL LETTER

Please refer to the FDA approved package insert for the full prescribing information of the drug product as follows:
• 0.9% Sodium Chloride Injection, USP (click https://www.dailymed.nlm.nih.gov/dailymed/getFile.cfm?setid=f55bd888-5e01-474d-871b-24654c070178&type=pdf&name=f55bd888-5e01-474d-871b-24654c070178)

Reporting Adverse Events or Product Quality Issues
To report adverse events associated with these imported products, please call Baxter at 1-866-888-2472, or fax: 1- 800-759-1801. Adverse events or quality problems experienced with the use of these imported products may also be reported to the FDA's MedWatch Adverse Event Reporting program either online, by regular mail or by fax:
• Complete and submit the report Online: www.fda.gov/medwatch/report.htm
• Regular mail or Fax: Download form www.fda.gov/MedWatch/getforms.htm or call 1-800-332-1088 to request a reporting form, then complete and return to the address on the pre-addressed form, or submit by fax to 1-800-FDA-0178 (1-800-332-0178).

To report product quality issues associated with these imported products, please contact Baxter Product Surveillance through Baxter Product Feedback Portal (https://productfeedback.baxter.com/)

PACKAGE/LABEL PRINCIPAL DISPLAY PANEL

Container Label

Baxter Logo Trademark

A6C1322

SODIUM CHLORIDE INJECTION

50

100

150

200

250ml
0.9% Sodium Chloride

[Strength] 250ml: 2.25g
[Description] This product is a clear, colorless liquid
[Dosage and Administration] Intravenous drip See the package
insert for details
For details of [Indications], [Adverse Reactions],
[Contraindications], and [Precautions], please refer to the
package insert

[Storage] Store in overwrap

The solution should be clear and should be used
up at one time
Inspect the inner bag by squeezing it and discard
solution if leakage occurs
License Number: H19994066

AA

[Drug Marketing Authorization Holder] [Manufacturer]
Name: Baxter Healthcare (Shanghai) Co., Ltd.
Address: No. 388, Tingzhu Road, Jinshan District, Shanghai

GTIN Barcode Area

LOT
MFG
EXP

Container Label

Baxter Logo Trademark

A6C1323

SODIUM CHLORIDE INJECTION

100

200

300

400

500ml
0.9% Sodium Chloride

[Strength] 500ml: 4.5g
[Description] This product is a clear, colorless liquid
[Dosage and Administration] Intravenous drip See the package
insert for details
For details of [Indications], [Adverse Reactions],
[Contraindications], and [Precautions], please refer to the
package insert

[Storage] Store in overwrap

The solution should be clear and should be used
up at one time
Inspect the inner bag by squeezing it and discard
solution if leakage occurs
License Number: H19983148

AA

[Drug Marketing Authorization Holder] [Manufacturer]
Name: Baxter Healthcare (Shanghai) Co., Ltd.
Address: No. 388, Tingzhu Road, Jinshan District, Shanghai

GTIN Barcode Area

LOT
MFG
EXP

Container Label

Baxter Logo Trademark

A6C1324

SODIUM CHLORIDE INJECTION

100

200

300

400

500

600

700

800

900

1000ml
0.9% Sodium Chloride

[Strength] 1000ml: 9g
[Description] This product is a clear, colorless liquid
[Dosage and Administration] Intravenous drip See the package
insert for details
For details of [Indications], [Adverse Reactions],
[Contraindications], and [Precautions], please refer to the
package insert

[Storage] Store in overwrap

The solution should be clear and should be used
up at one time
Inspect the inner bag by squeezing it and discard
solution if leakage occurs
License Number: H19983149

AA

[Drug Marketing Authorization Holder] [Manufacturer]
Name: Baxter Healthcare (Shanghai) Co., Ltd.
Address: No. 388, Tingzhu Road, Jinshan District, Shanghai

GTIN Barcode Area

LOT
MFG
EXP